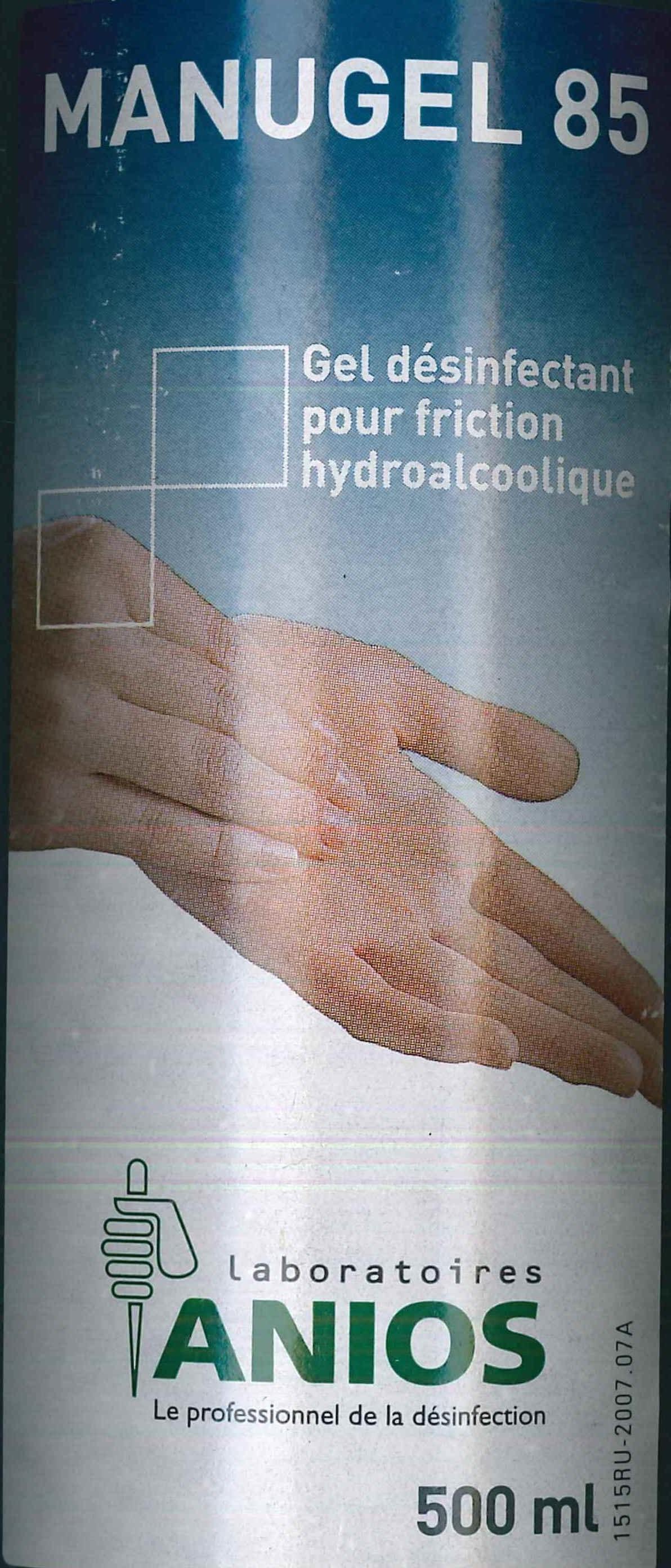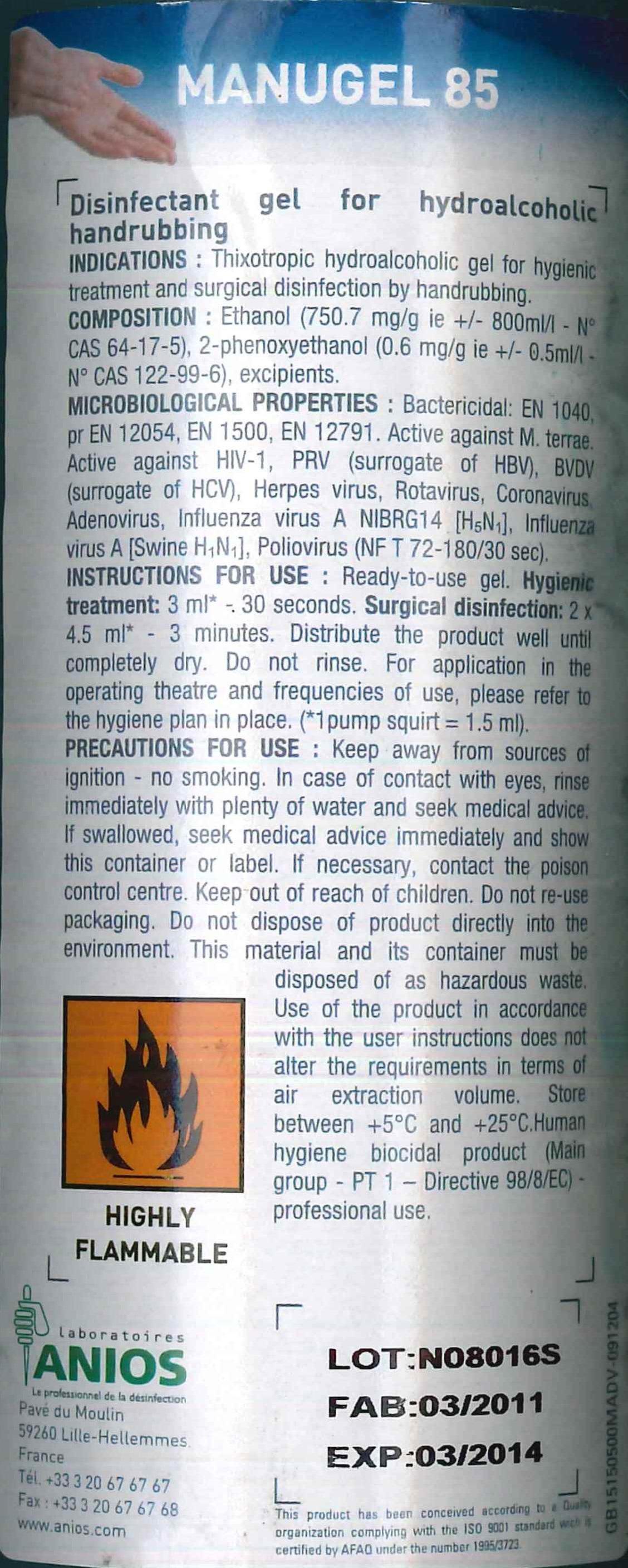 DRUG LABEL: MANUGEL 85
NDC: 62169-202 | Form: GEL
Manufacturer: Laboratoires Anios
Category: otc | Type: HUMAN OTC DRUG LABEL
Date: 20140331

ACTIVE INGREDIENTS: ALCOHOL 400 mL/500 mL; PHENOXYETHANOL 0.3 g/500 mL
INACTIVE INGREDIENTS: Glycerin 99.7 mL/500 mL

INDICATIONS AND USAGE

Thixotropic hydroalcoholic gel for hygienic treatment and surgical disinfetion by hand-rubbing.

ACTIVE INGREDIENT

Ethanol (700 mg/g ie 755 ml/l - N° CAS 64-17-5) in the presence of thickening, moisturizing and emollient agents, and water. Without purfume nor coloring.

MICROBIOLOGY

Bactericidal: EN 1040, pr EN 12054, EN 1500, EN 12791. Tuberculocidal: EN 14348. Yeasticidal EN 1275, EN 1650. Virucidal: EN 14476+A1 (30 sec.). Active against HIV-1, PRV (surrogate of HBV), BVDV (surrogate of HCV), Rotavirus, Herpes virus, Coronavirus, Norovirus, Influenza virus A [H1N1] and Influenca virus A NIBRG14 [H5N1].

INSTRUCTIONS FOR USE

A ready-to-use gel. Hygienic treatment: 3 ml* for a hand-rubbing time of 30 seconds. Surgical disinfection: 2 x 3 ml* for a hand-rubbing time of two times 45 seconds. Well-apply and rub until complete dry. Do not rinse. (*3 ml = 2 pump squirts). For application in operating theater and frequency of use, refer to the protocol of the establishment.

DOSAGE AND ADMINISTRATION

Hygienic treatment: 3 ml* for a hand-rubbing time of 30 seconds. Surgical disinfection: 2 x 3 ml* for a hand-rubbing time of two times 45 seconds. Well-apply and rub until complete dry. Do not rinse. (*3 ml = 2 pump squirts).

WARNINGS AND PRECAUTIONS

Topical route exclusively. Flammable. Keep away from sources of ignition - no smoking. Avoid contact with eyes. In case of contact with eyes, rinse immediately with plenty of water and seek medical advice. If swallowed, seek medical advice immediately and show this container or label. If necessary, contact the poison control center. Keep out of reach of children. Do not dispose of product directly into the environment. Do not reuse the packaging. This material and the container must be disposed of in a safe way. Use of the product in accordance with the use instructions does not alter the requirements in terms of air extraction volume. Storage: from +5°C to +25°C. Human hygiene biocidal product (Main Group 1 - PT1 - directive 98/8/EC). Professional use. Made in France.

Keep out of reach of children.

PURPOSE

Thixotropic hydroalcoholic gel for hygienic treatment and surgical disinfetion by hand-rubbing

Active ingredient in the presence of thickening, moisturizing and emollient agents, and water. Without purfume nor coloring.

WARNINGS

Topical route exclusively. Flammable. Keep away from sources of ignition - no smoking. Avoid contact with eyes. In case of contact with eyes, rinse immediately with plenty of water and seek medical advice. If swallowed, seek medical advice immediately and show this container or label. If necessary, contact the poison control center. Keep out of reach of children. Do not dispose of product directly into the environment. Do not reuse the packaging. This material and the container must be disposed of in a safe way. Use of the product in accordance with the use instructions does not alter the requirements in terms of air extraction volume. Storage: from +5°C to +25°C. Human hygiene biocidal product (Main Group 1 - PT1 - directive 98/8/EC). Professional use. Made in France.